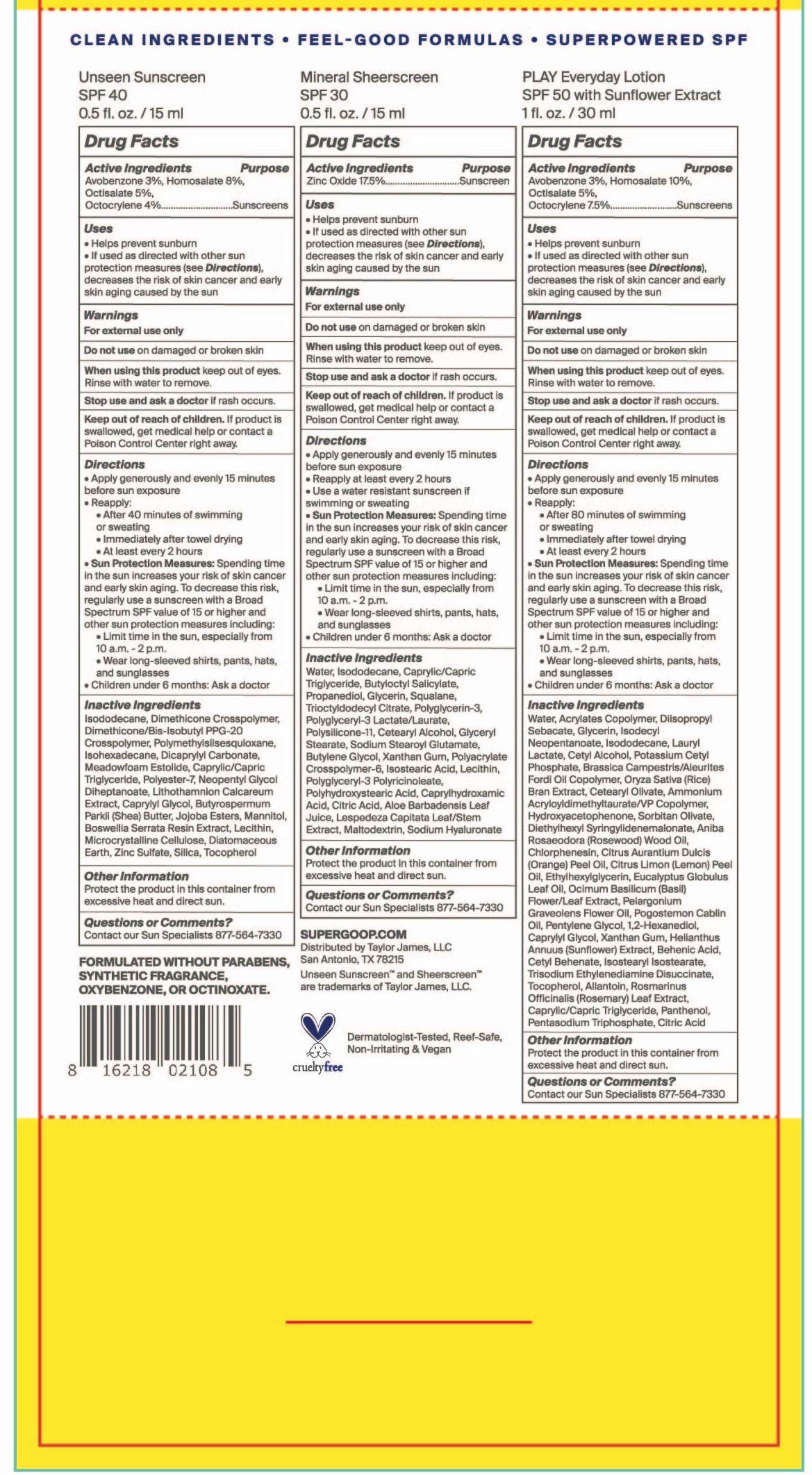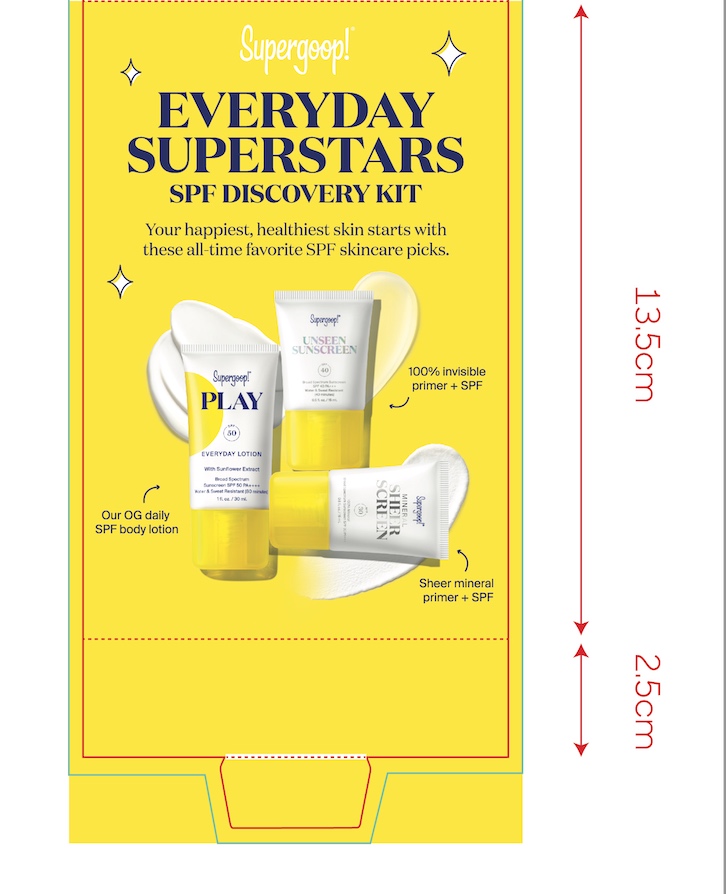 DRUG LABEL: Everyday Superstars SPF Discovery Kit
NDC: 82384-0034 | Form: KIT | Route: TOPICAL
Manufacturer: System Beauty, LLC
Category: otc | Type: HUMAN OTC DRUG LABEL
Date: 20211216

ACTIVE INGREDIENTS: OCTOCRYLENE 4 g/100 mL; AVOBENZONE 3 g/100 mL; OCTISALATE 5 g/100 mL; HOMOSALATE 8 g/100 mL; ZINC OXIDE 17.5 g/100 mL; OCTISALATE 5 g/100 mL; AVOBENZONE 3 g/100 mL; HOMOSALATE 10 g/100 mL; OCTOCRYLENE 7.5 g/100 mL
INACTIVE INGREDIENTS: LECITHIN, SUNFLOWER; SHEA BUTTER; SILICON DIOXIDE; NEOPENTYL GLYCOL DIHEPTANOATE; PHYMATOLITHON CALCAREUM; ZINC SULFATE, UNSPECIFIED FORM; DIATOMACEOUS EARTH; TOCOPHEROL; MANNITOL; DIMETHICONE/BIS-ISOBUTYL PPG-20 CROSSPOLYMER; POLYESTER-7; MEDIUM-CHAIN TRIGLYCERIDES; ISODODECANE; DIMETHICONE CROSSPOLYMER (450000 MPA.S AT 12% IN CYCLOPENTASILOXANE); POLYMETHYLSILSESQUIOXANE (11 MICRONS); ISOHEXADECANE; DICAPRYLYL CARBONATE; CAPRYLYL GLYCOL; INDIAN FRANKINCENSE; MICROCRYSTALLINE CELLULOSE; DIMETHICONE/VINYL DIMETHICONE CROSSPOLYMER (SOFT PARTICLE); CETOSTEARYL ALCOHOL; ISODODECANE; MEDIUM-CHAIN TRIGLYCERIDES; BUTYLOCTYL SALICYLATE; ALOE VERA LEAF; HYALURONATE SODIUM; TRIOCTYLDODECYL CITRATE; POLYGLYCERIN-3; GLYCERIN; SQUALANE; AMMONIUM ACRYLOYLDIMETHYLTAURATE, DIMETHYLACRYLAMIDE, LAURYL METHACRYLATE AND LAURETH-4 METHACRYLATE COPOLYMER, TRIMETHYLOLPROPANE TRIACRYLATE CROSSLINKED (45000 MPA.S); POLYHYDROXYSTEARIC ACID (2300 MW); CAPRYLHYDROXAMIC ACID; LESPEDEZA CAPITATA FLOWERING TOP; GLYCERYL MONOSTEARATE; LECITHIN, SOYBEAN; MALTODEXTRIN; WATER; PROPANEDIOL; SODIUM STEAROYL GLUTAMATE; XANTHAN GUM; ISOSTEARIC ACID; POLYGLYCERYL-3 PENTARICINOLEATE; CITRIC ACID MONOHYDRATE; CETEARYL OLIVATE; LAURYL LACTATE; AMMONIUM ACRYLOYLDIMETHYLTAURATE/VP COPOLYMER; CAPRYLYL GLYCOL; LEMON OIL, COLD PRESSED; DIETHYLHEXYL SYRINGYLIDENEMALONATE; ROSEWOOD OIL; ORANGE OIL, COLD PRESSED; POGOSTEMON CABLIN LEAF OIL; 1,2-HEXANEDIOL; ISOSTEARYL ISOSTEARATE; TRISODIUM ETHYLENEDIAMINE DISUCCINATE; TOCOPHEROL; ALLANTOIN; ROSEMARY; WATER; DIISOPROPYL SEBACATE; GLYCERIN; HYDROXYACETOPHENONE; SORBITAN OLIVATE; POTASSIUM CETYL PHOSPHATE; ETHYLHEXYLGLYCERIN; BEHENIC ACID; MEDIUM-CHAIN TRIGLYCERIDES; PENTYLENE GLYCOL; ISODECYL NEOPENTANOATE; ISODODECANE; CETYL ALCOHOL; RICE BRAN; XANTHAN GUM; HELIANTHUS ANNUUS FLOWERING TOP; CETYL BEHENATE; CHLORPHENESIN; EUCALYPTUS OIL; OCIMUM BASILICUM FLOWERING TOP; PELARGONIUM GRAVEOLENS FLOWER OIL; PANTHENOL; SODIUM TRIPOLYPHOSPHATE ANHYDROUS; CITRIC ACID MONOHYDRATE

Everyday Superstars SPF Discovery Kit

Unseen Sunscreen Active Ingredients

Active Ingredients Purpose

Avobenzone 3% Sunscreen

Homosalate 8% Sunscreen

Octocrylene 4% Sunscreen

Octisalate 5% Sunscreen

Mineral Sheerscreen SPF 30 Active ingredients

Active Ingredient Purpose

Zinc Oxide 17.5% Sunscreen

Play Everyday Sunscreen SPF 50 with Sunflower Extract Active ingredient

Active Ingredients Purpose

Avobenzone 3% Sunscreen

Homosalate 10% Sunscreen

Octisalate 5% Sunscreen

Octocrylene 7.5% Sunscreen

Uses

Helps Prevent Sunburn

If used as directed with other sun protection measures (see Directions), decreases the risk of Skin cancer and early skin aging caused by the sun

Keep out of reach of children. If swallowed, get medical help or contact a Poison Control Center right away

Unseen sunscreen SPF 40

Directions

- apply generously and evenly 15 minutes before sun exposure
- reapply:

after 40 minutes of swimming or sweating

immediately after towel drying

at least every 2 hours

- Sun Protection Measures Spending time in the sun increases your risk of skin cancer and early skin aging. To decrease this risk, regularly use a sunscreen with a Broad Spectrum SPF value of 15 or higher and other sun protection measures including:
- Limit time in the sun, especially from 10 a.m.-2 p.m.
- Wear long-sleeved shirts, pants, hats, and sunglasses
- Children under 6 months: ask a doctor

Mineral Sheerscreen SPF 30 directions

- apply generously and evenly 15 minutes before sun exposure
- reapply at least every 2 hours

use a water resistant sunscreen if swimming or sweating

- Sun Protection Measures: Spending time in the sun increases your risk of skin cancer and early skin aging. To decrease this risk, regularly use a sunscreen with a Broad Spectrum SPF value of 15 or higher and other sun protection measures including:
- Limit time in the sun, especially from 10 a.m. - 2 p.m.
- Wear long-sleeved shirts, pants, hats, and sunglassess
- Children under 6 months: Ask a doctor.

Play Everyday Sunscreen SPF 50 with Sunflower Extract directions

Directions

- Apply liberally 15 minutes before sun exposure

Reapply:

- after 80 minutes of swimming or sweating
- immediately after towel drying
- at least every 2 hours
- Sun Protection Measures. Spending time in the sun increases your risk of skin

cancer and early skin aging. To decrease this risk, regularly use a sunscreen
with broad spectrum SPF of 15 or higher and other sun protection measures
including:

- limit time in the sun, especially from 10 a.m. - 2 p.m.
- Wear Long-sleeved shirts, pants, hats, and sunglasses
- Children under 6 months: Ask a doctor

Unseen Sunscreen SPF 40 Inactive ingredients

Inactive Ingredients

Isododecane, Dimethicone Crosspolymer, Dimethicone/Bis-Isobutyl PPG-20 Crosspolymer, Polymethylsilsesquioxane, Isohexadecane, Dicrapylyl Carbonate, Meadowfoam Estolide, Caprylic/Capric Triglyceride, Polyester-7, Neopentyl Glycol Diheptanoate, Lithothamnion Calcareum Extract,Butyrospermum Parkii (Shea) Butter, Jojoba Esters, Mannitol, Boswellia Serrata Resin Extract, Lecithin, Microcrystalline Cellulose, Diatomaceous Earth, Zinc Sulfate, Silica, Tocopherol

Mineral Sheerscreen Inactive ingredients

Water, Isododecane, Caprylic/Capric Triglyceride, Butyloctyl Salicylate, Propanedlol, Glycerin, Squalane, Trioctyldodecyl Citrate, Polyglycerln-3, Polyglyceryl-3 Lactate/Laurate, Polysilicone-11, Cetearyl Alcohol, Glyceryl Stearate, Sodium Stearoyl Glutamate, Butylene Glycol, Xanthan Gum, Polyacrylate Crosspolymer-6, lsostearic Acid, Lecithin, Polyglyceryl-3 Polyricinoleate, Polyhydroxystearic Acid, Caprylhydroxamic Acid, Citric Acid, Aloe Barbadensis Leaf Juice, Lespedeza Capitata Leaf/Stem Extract, Maltodextrin, Sodium Hyaluronate

Play Everyday Lotion SPF 50 with Sunflower Extract Inactive ingredients

Water, Acrylates Copolymer, Diisopropyl Sebacate, Glycerin, Isodecyl Neopentanoate, Isododecane, Lauryl Lactate, Cetyl Alcohol, Potassium Cetyl Phosphate, Brassica Camprestris/Aleurites Fordi Copolymer, Oryza Sativa (Rice) Bran Extract, Cetearyl Olivate, Ammonium Acryloyldimethyltaurate/VP Copolymer, Hydroxyacetophenone, Sorbitan Olivate, Diethylhexyl Syringylidenemalonate, Aniba Rosaeodora (Rosewood) Wood Oil, Chlorphenesin, Citrus Aurantium Dulcis (Orange) Peel Oil, Citrus Limon (Lemon) Peel Oil, Ethylhexylglycerin, Eucalyptus Globulus Leaf Oil, Ocimum Bascilicum (Basil) Flower/Leaf Extract, Pelargonium Graveolens Flower Oil, Pogostemon Cablin Oil, Pentylene Glycol, 1,2-hexanediol, Caprylyl Glycol, Xanthan Gum, Helianthus Annuus (Sunflower) Extract, Behenic Acid, Cetyl Behenate, Isostearyl Isostearate, Trisodium Ethylenediamene Disuccinate, Tocopherol, Allantoin, Rosmarinus Officinalis (Rosemary) Leaf Extract, Caprylic/Capric Triglyceride,Panthenol, Pentasodium Triphosphate, Citric Acid

PACKAGE LABEL

Everyday Superstars SPF Discovery Kit

Your happiest, healthiest skin starts with these all-time favorite SPF skincare picks

Unseen Sunscreen SPF 40

0.5 fl oz./ 15 ml

Mineral Sheerscreen SPF 30

0.5 fl. oz. / 15 ml

PLAY Everyday Lotion SPF 50 with Sunflower Extract

1 fl. oz. / 30 ml